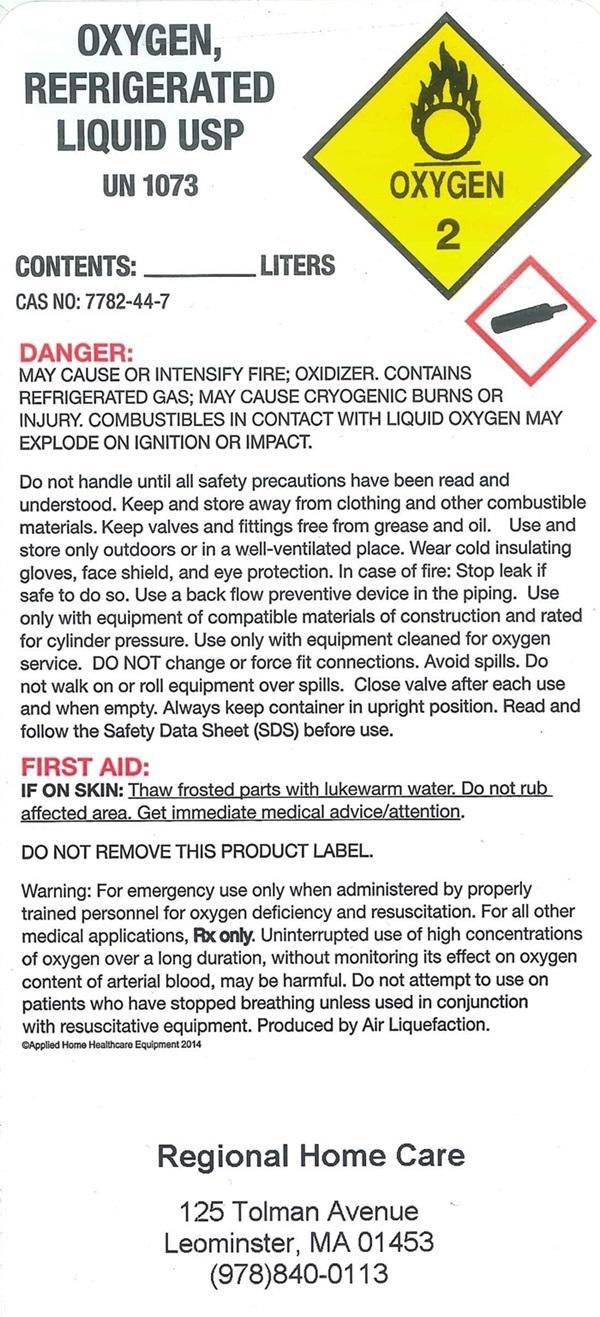 DRUG LABEL: OXYGEN
NDC: 53622-001 | Form: GAS
Manufacturer: Regional Home Care, Inc.
Category: prescription | Type: HUMAN PRESCRIPTION DRUG LABEL
Date: 20251024

ACTIVE INGREDIENTS: OXYGEN 99 L/100 L

OXYGEN REFRIGERATED LIQUID USP LABEL

OXYGEN REFRIGERATED LIQUID USP UN1073

CONTENTS_________ LITERS

CAS NO: 7782-44-7

DANGER:
MAY CAUSE OR INTENSIFY FIRE; OXIDIZER. CONTAINS REFRIGERATED GAS; MAY CAUSE CRYOGENIC BURNS OR INJURY. COMBUSTIBLES IN CONTACT WITH LIQUID OXYGEN MAY EXPLODE ON IGNITION OR IMPACT.

Do not handle until all safety precautions have been read and understood. Keep and store away from clothing and other combustible materials. Keep valves and fittings free from grease and oil. Use and store only outdoors or in a well-ventilated place. Wear cold insulating gloves, face shield, and eye protection. In case of fire: Stop leak if safe to do so. Use a back flow preventive device in the piping. Use only with equipment of compatible materials of construction and rated for cylinder pressure. Use only with equipment cleaned for oxygen service. DO NOT change or force fit connections. Avoid spills. Do not walk or roll equipment over spills. Close valve after each use and when empty. Always keep container in upright position. Read and follow the Safety Data Sheet (SDS) before use.

FIRST AID:

IF ON SKIN:Thaw frosted parts with lukewarm water. Do not rub affected area. Get immediate medical advise/attention.

DO NOT REMOVE THIS PRODUCT LABEL

Warning: For emergency use only when administered by properly trained personnel for oxygen deficiency and resuscitation. For all other medical applications, Rx only. Uninterrupted use of high concentrations of oxygen over a long duration, without monitoring its effect on oxygen content in arterial blood, may be harmful. Do not attempt to use on patients who have stopped breathing unless used in conjunction with resuscitative equipment. Producted by Air Liquefaction.

©Applied Hone Health Equipment 2014

Regional Home Care

125 Tolman Avenue

Leominster, MA 01453

(978)840-0113

res